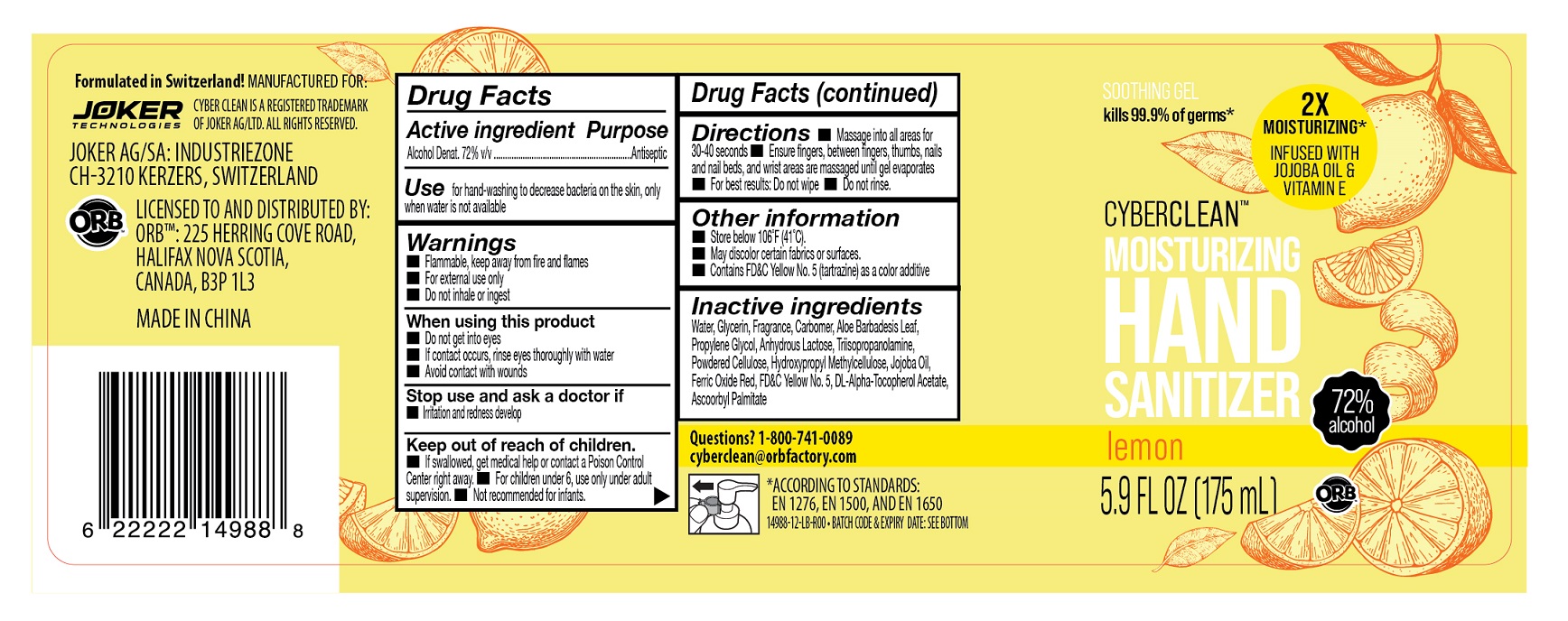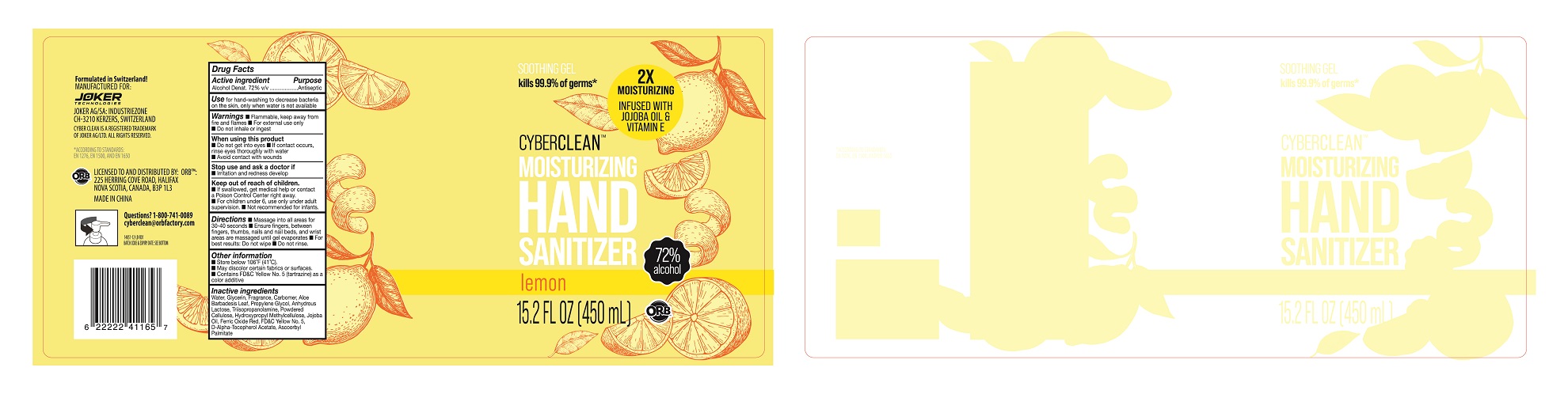 DRUG LABEL: Cyber Clean Moisturizing Hand Sanitizer Lemon
NDC: 75757-116 | Form: LIQUID
Manufacturer: JOKER AG
Category: otc | Type: HUMAN OTC DRUG LABEL
Date: 20210126

ACTIVE INGREDIENTS: ALCOHOL 72 mL/100 mL
INACTIVE INGREDIENTS: CARBOMER 980; TRIISOPROPANOLAMINE; FD&C YELLOW NO. 5; HYPROMELLOSES; ALPHA-TOCOPHEROL ACETATE; ANHYDROUS LACTOSE; JOJOBA OIL; FERRIC OXIDE YELLOW; GLYCERIN; ALOE VERA LEAF; WATER; PROPYLENE GLYCOL; ASCORBYL PALMITATE; POWDERED CELLULOSE

Cyber Clean Moisturizing Hand Sanitizer Lemon

Cyber Clean Moisturizing Hand Sanitizer Lemon

Active Ingredient(s)

Alcohol 72% v/v. Purpose: Antiseptic

Purpose

Antiseptic, Hand Sanitizer

Use

Hand Sanitizer to help reduce bacteria that potentially can cause disease. For use when soap and water are not available.

Warnings

For external use only. Flammable. Keep away from heat or flame

Do not use

- in children less than 2 months of age
- on open skin wounds

When using this product keep out of eyes, ears, and mouth. In case of contact with eyes, rinse eyes thoroughly with water.
Stop use and ask a doctor if irritation or rash occurs. These may be signs of a serious condition.
Keep out of reach of children. If swallowed, get medical help or contact a Poison Control Center right away.

Stop use and ask a doctor if irritation or rash occurs. These may be signs of a serious condition.

Keep out of reach of children. If swallowed, get medical help or contact a Poison Control Center right away.

Directions

- Place enough product on hands to cover all surfaces. Rub hands together until dry.
- Supervise children under 6 years of age when using this product to avoid swallowing.

Other information

- Store between 15-30C (59-86F)
- Avoid freezing and excessive heat above 40C (104F)

Inactive ingredients

Water
Glycerol
Aloe barbadensis leaf extract
Propylene Glycol
Carbomer 980
Triisopropanolamine
FD&C Yellow 5
Lactose
Cellulose
Hydroxypropyl methylcellulose
Jojoba Esters
Iron oxides
Tocopheryl acetate
Ascorbyl Palmitate